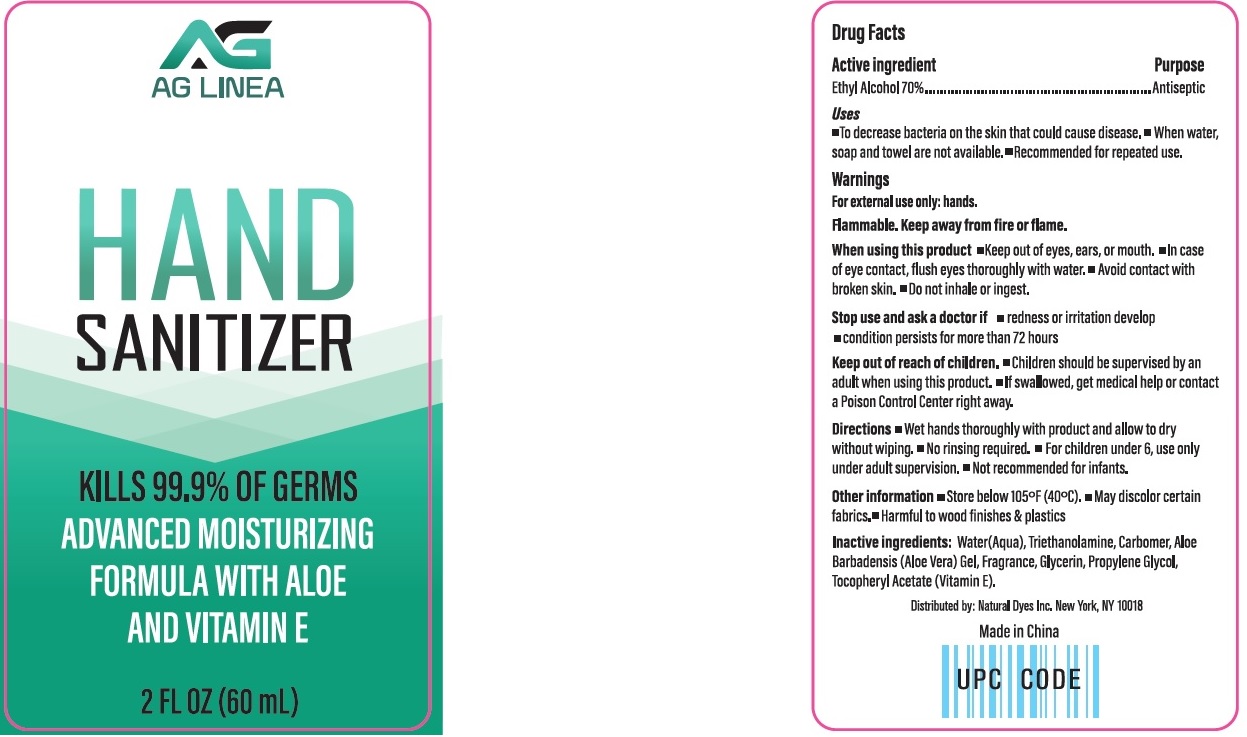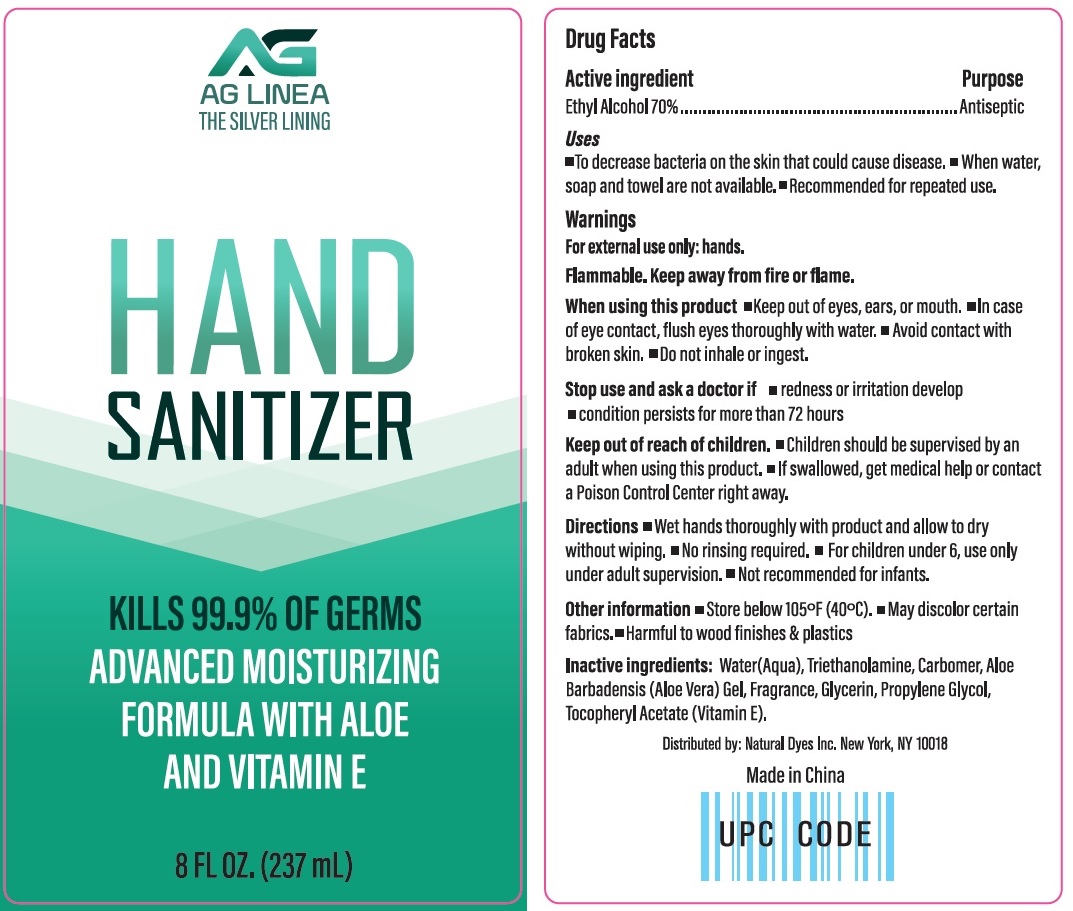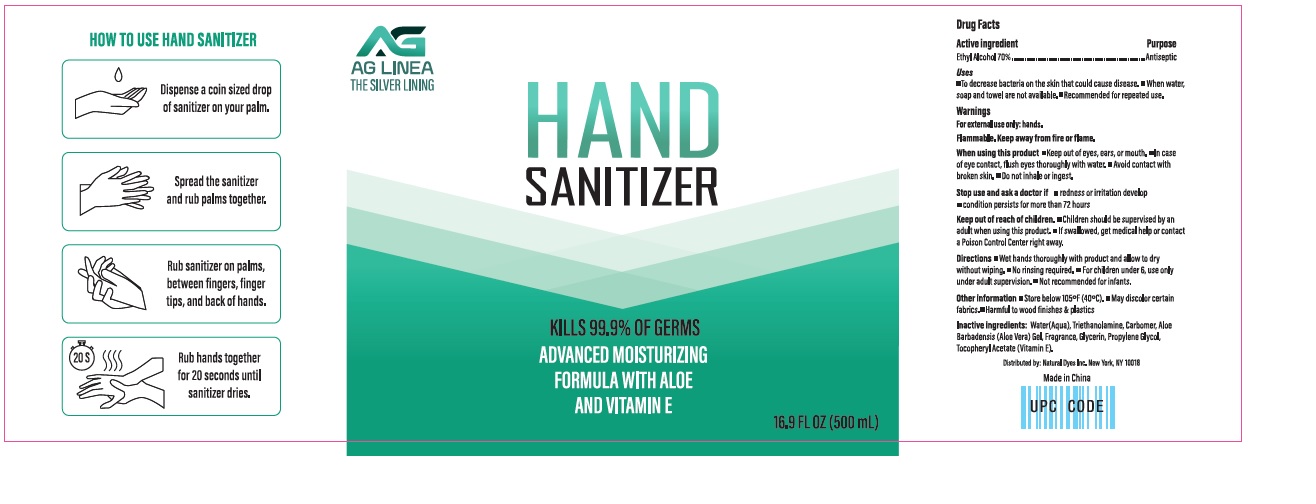 DRUG LABEL: AG LINEA HAND SANITIZER
NDC: 77781-001 | Form: GEL
Manufacturer: Natural Dyes Inc
Category: otc | Type: HUMAN OTC DRUG LABEL
Date: 20200811

ACTIVE INGREDIENTS: Alcohol 70 mL/100 mL
INACTIVE INGREDIENTS: WATER; TROLAMINE; CARBOMER HOMOPOLYMER, UNSPECIFIED TYPE; ALOE VERA LEAF; GLYCERIN; PROPYLENE GLYCOL; .ALPHA.-TOCOPHEROL ACETATE

AG LINEA HAND SANITIZER

Active ingredient

Ethyl Alcohol 70%

Purpose

Antiseptic

Uses

- To decrease bacteria on the skin that could cause disease.
- When water, soap and towel are not available.
- Recommended for repeated use.

Warnings

For external use only: hands.

Flammable. Keep away from fire or flame.

When using this product • Keep out of eyes, ears, or mouth. • In case of eye contact, flush eyes thoroughly with water. • Avoid contact with broken skin. • Do not inhale or ingest.

Stop use and ask a doctor if • redness or irritation develop

• condition persists for more than 72 hours

Keep out of reach of children.

• Children should be supervised by an adult when using this product. • If swallowed, get medical help or contact a Poison Control Center right away.

Directions

• Wet hand thoroughly with product and allow to dry without wiping. • No rinsing required. • For children under 6, use only under adult supervision. • Not recommended for infants.

Other information

• Store below 105˚F(40˚C). • May discolor certain fabrics. • Harmful to wood finishes & plastics

Inactive ingredients:

Water(Aqua), Triethanolamine, Carbomer, Aloe Barbadensis(Aloe Vera) Gel, Fragrance, Glycerin, Propylene Glycol, Tocopheryl Acetate(Vitamin E).

Distributed by:

Natural Dyes Inc.

New York, NY 10018

Made in China

UPC CODE

Kills 99.9% of Germs

ADVANCED MOISTURIZING FORMULA WITH ALOE AND VITAMIN E

HOW TO USE HAND SANITIZER

Dispense a coin sized drop of sanitizer on your palm.

Spread the sanitizer and rub palms together.

Rub sanitizer on palms, between fingers, finger tips, and back of hands.

Rub hands together for 20 seconds until sanitizer dries.